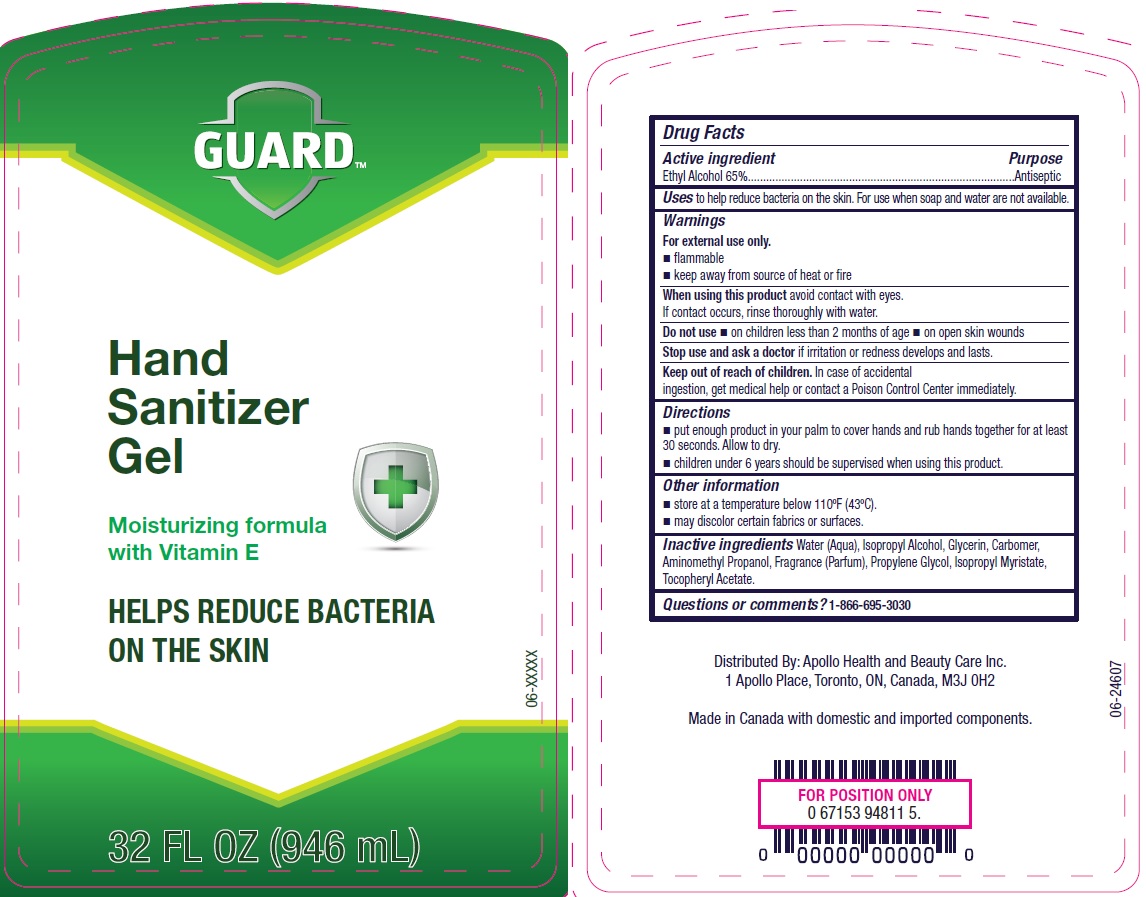 DRUG LABEL: Guard Hand Sanitizer
NDC: 63148-515 | Form: GEL
Manufacturer: Apollo Health and Beauty Care Inc.
Category: otc | Type: HUMAN OTC DRUG LABEL
Date: 20200420

ACTIVE INGREDIENTS: ALCOHOL 650 mg/1 mL
INACTIVE INGREDIENTS: WATER; ISOPROPYL ALCOHOL; GLYCERIN; ISOPROPYL MYRISTATE; ALOE VERA LEAF; .ALPHA.-TOCOPHEROL ACETATE, DL-; CARBOMER 934; AMINOMETHYLPROPANOL

Drug Facts

Active ingredient

Ethyl Alcohol 65%

Purpose

Antiseptic

Uses

to help reduce bacteria on the skin . For use when soap and water are not available.

Warnings

For external use only

- flammable
- keep away from source of heat or fire

When using this product

avoid contact with eyes. If contact occurs, rinse thoroughly with water.

Do not use

- on children less than 2 months of age
- on open skin wounds

Stop use and ask a doctor if

irritation or redness develops and lasts.

Keep out of reach of children.

In case of accidental ingestion, get medical help or contact a Poison Control Center immediately.

Directions

- put enough product in your palm to cover hands and rub hands together for at least 30 seconds. Allow to dry.
- children under 6 years should be supervised when using this product.

Other information

- store at a temperature below 110°F (43°C)
- may discolor certain fabrics or surfaces

Inactive ingredients

Water (Aqua), Isopropyl Alcohol, Glycerin, Isopropyl Myristate, Aloe Barbadensis Leaf Juice, Tocopheryl Acetate, Carbomer, Aminomethyl Propanol, Fragrance (Parfum).

Questions or comments?

1-866-695-3030